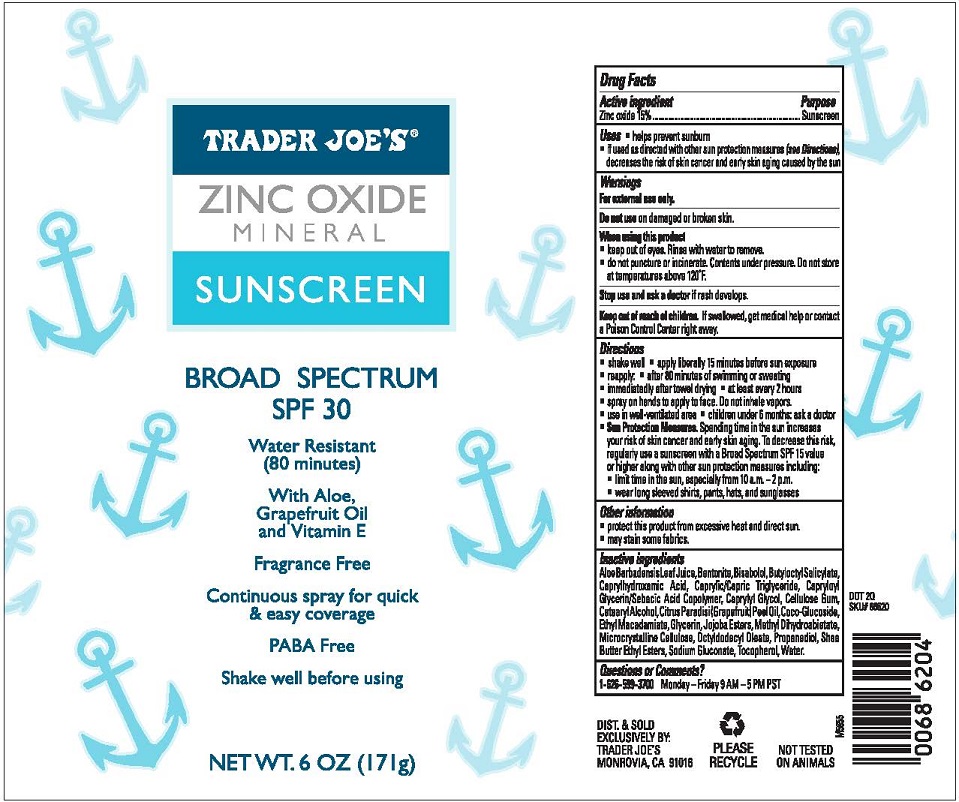 DRUG LABEL: TRADER JOES ZINC OXIDE MINERAL SUNSCREEN
NDC: 71270-155 | Form: SPRAY
Manufacturer: Trader Joe's Company
Category: otc | Type: HUMAN OTC DRUG LABEL
Date: 20241022

ACTIVE INGREDIENTS: ZINC OXIDE 15 g/100 g
INACTIVE INGREDIENTS: ALOE VERA LEAF; BENTONITE; .ALPHA.-BISABOLOL, (+)-; BUTYLOCTYL SALICYLATE; CAPRYLHYDROXAMIC ACID; MEDIUM-CHAIN TRIGLYCERIDES; CAPRYLOYL GLYCERIN/SEBACIC ACID COPOLYMER (2000 MPA.S); CAPRYLYL GLYCOL; CARBOXYMETHYLCELLULOSE SODIUM (0.7 CARBOXYMETHYL SUBSTITUTION PER SACCHARIDE; 1200 MPA.S AT 1%); CETOSTEARYL ALCOHOL; GRAPEFRUIT PEEL; COCO GLUCOSIDE; ETHYL MACADAMIATE; GLYCERIN; HYDROGENATED JOJOBA OIL/JOJOBA OIL, RANDOMIZED (IODINE VALUE 40-44); METHYL DIHYDROABIETATE; MICROCRYSTALLINE CELLULOSE; OCTYLDODECYL OLEATE; PROPANEDIOL; SHEA BUTTER; SODIUM GLUCONATE; TOCOPHEROL; WATER

TRADER JOE’S (as PLD) - ZINC OXIDE SUNSCREEN BROAD SPECTRUM SPF 30 (71270-155)

Active ingredient

Zinc Oxide 15%

Purpose

Sunscreen

Uses

- Helps prevent sunburn.
- If used as directed with other sun protection measures (See Directions), decreases the risk of skin cancer and early skin aging caused by the sun.

Warnings

For external use only.

Do not useon damaged or broken skin.

When using this product

- keep out of eyes. Rinse with water to remove.
- Do not puncture or incinerate. Contents under pressure. Do not store at temperatures above 120°F.

Stop use and ask a doctorif rash occurs.

Keep out of reach of children.If swallowed, get medical help or contact a Poison Control Center immediately.

Directions

- Shake well
- Apply liberally 15 minutes before sun exposure.
- Reapply
- after 40 minutes of swimming or sweating
- immediately after towel drying
- at least every 2 hours.
- Spray on hands to apply to face. Do not inhale vapors.
- Use in a well-ventilated area
- Children under 6 months: ask a doctor.

Sun Protection Measures.Spending time in the sun increases your risk of skin cancer and early skin aging. To decrease this risk, regularly use a sunscreen with a Broad Spectrum SPF 15 value or higher along with other sun protection measures including:

- limit time in the sun, especially from 10 a.m. – 2 p.m.
- wear long sleeved shirts, pants, hats and sunglasses.

Other information

- Protect the product in this container from excessive heat and direct sun
- May stain some fabrics.

Inactive ingredients

ALOE BARBADENSIS LEAF JUICE, BENTONITE, BISABOLOL, BUTYLOCTYL SALICYLATE, CAPRYLHYDROXAMIC ACID, CAPRYLIC/CAPRIC TRIGLYCERIDE, CAPRYLOYL GLYCERIN/SEBACIC ACID COPOLYMER, CAPRYLYL GLYCOL, CELLULOSE GUM, CETEARYL ALCOHOL, CITRUS PARADISI (GRAPEFRUIT) PEEL OIL, COCO-GLUCOSIDE, ETHYL MACADAMIATE, GLYCERIN, JOJOBA ESTERS, METHYL DIHYDROABIETATE, MICROCRYSTALLINE CELLULOSE, OCTYLDODECYL OLEATE, PROPANEDIOL, SHEA BUTTER ETHYL ESTERS, SODIUM GLUCONATE, TOCOPHEROL, WATER.

Questions or comments?

1- 626-599-3700Monday – Friday 9 AM – 5 PM PST